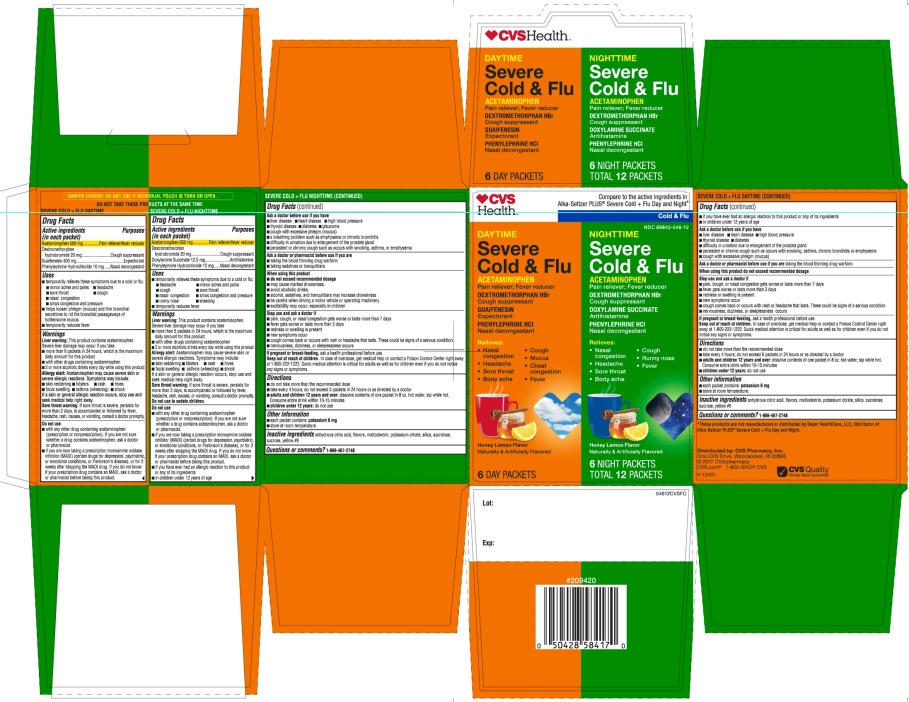 DRUG LABEL: SEVERE COLD PLUS FLU DAYTIME NIGHTTIME
NDC: 69842-546 | Form: KIT | Route: ORAL
Manufacturer: CVS Pharmacy,Inc.
Category: otc | Type: HUMAN OTC DRUG LABEL
Date: 20251208

ACTIVE INGREDIENTS: ACETAMINOPHEN 500 mg/1 1; DEXTROMETHORPHAN HYDROBROMIDE 20 mg/1 1; GUAIFENESIN 400 mg/1 1; PHENYLEPHRINE HYDROCHLORIDE 10 mg/1 1; ACETAMINOPHEN 650 mg/1 1; DEXTROMETHORPHAN HYDROBROMIDE 20 mg/1 1; DOXYLAMINE SUCCINATE 12.5 mg/1 1; PHENYLEPHRINE HYDROCHLORIDE 10 mg/1 1
INACTIVE INGREDIENTS: ANHYDROUS CITRIC ACID; MALTODEXTRIN; POTASSIUM CITRATE; SILICON DIOXIDE; SUCRALOSE; SUCROSE; FD&C YELLOW NO. 6; ANHYDROUS CITRIC ACID; MALTODEXTRIN; POTASSIUM CITRATE; SILICON DIOXIDE; SUCRALOSE; SUCROSE; FD&C YELLOW NO. 6

CVS Health™Severe Cold & Flu Daytime and Nighttime

SEVERE COLD + FLU DAYTIME

Drug Facts

ACTIVE INGREDIENT

PURPOSE

Active ingredients (in each packet) | Purposes
Acetaminophen 500 mg | Pain reliever/fever reducer
Dextromethorphan hydrobromide 20 mg | Cough suppressant
Guaifenesin 400 mg | Expectorant
Phenylephrine hydrochloride 10 mg | Nasal decongestant

Uses

- temporarily relieves these symptoms due to a cold or flu:
  - minor aches and pains
  - headache
  - sore throat
  - cough
  - nasal congestion
  - sinus congestion and pressure
- helps loosen phlegm (mucus) and thin bronchial secretions to rid the bronchial passageways of bothersome mucus
- temporarily reduces fever

Warnings

Liver warning

This product contains acetaminophen. Severe liver damage may occur if you take

- more than 6 packets in 24 hours, which is the maximum daily amount for this product
- with other drugs containing acetaminophen
- 3 or more alcoholic drinks every day while using this product

ALLERGY ALERT

- Acetaminophen may cause severe skin or severe allergic reactions. Symptoms may include:
- Is a skin or general allergic reaction occurs, stop use and seek medical help right away.

- Skin reddening
- Blisters
- Rash
- Hives
- facial swelling
- asthma(wheezing)
- shock
  Is a skin or general allergic reaction occurs, stop use and seek medical help right away.

Sore throat warning

If sore throat is severe, persists for more than 2 days, is accompanied or followed by fever, headache, rash, nausea, or vomiting, consult a doctor promptly.

Do not use

- with any other drug containing acetaminophen (prescription or nonprescription). If you are not sure whether a drug contains acetaminophen, ask a doctor or pharmacist.
- if you are now taking a prescription monoamine oxidase inhibitor (MAOI) (certain drugs for depression, psychiatric, or emotional conditions, or Parkinson's disease), or for 2 weeks after stopping the MAOI drug. If you do not know if your prescription drug contains an MAOI, ask a doctor or pharmacist before taking this product.
- if you have ever had an allergic reaction to this product or any of its ingredients
- in children under 12 years of age

Ask a doctor before use if you have

- liver disease
- heart disease
- high blood pressure
- thyroid disease
- diabetes
- difficulty in urination due to enlargement of the prostate gland
- persistent or chronic cough such as occurs with smoking, asthma, chronic bronchitis or emphysema
- cough with excessive phlegm (mucus)

Ask a doctor or pharmacist before use if you aretaking the blood thinning drug warfarin

When using this product do not exceed recommended dosage

Stop use and ask a doctor if

- pain, cough, or nasal congestion gets worse or lasts more than 7 days
- fever gets worse or lasts more than 3 days
- redness or swelling is present
- new symptoms occur
- cough comes back or occurs with rash or headache that lasts. These could be signs of a serious condition.
- nervousness, dizziness, or sleeplessness occurs

PREGNANCY OR BREAST FEEDING

If pregnant or breast-feeding,ask a health professional before use.

Keep out of reach of children.In case of overdose, get medical help or contact a Poison Control Center right away at 1-800-222-1222. Quick medical attention is critical for adults as well as for children even if you do not notice any signs or symptoms.

Directions

- do not take more than the recommended dose
- take every 4 hours; do not exceed 6 packets in 24 hours or as directed by a doctor
- adults and children 12 years and over: dissolve contents of one packet in 8 oz. hot water; sip while hot. Consume entire drink within 10-15 minutes.
- children under 12 years: do not use

Other information

- each packet contains: potassium 6 mg
- store at room temperature

Inactive ingredients

anhydrous citric acid, flavors, maltodextrin, potassium citrate, silica, sucralose, sucrose, yellow#6

Questions or comments?

1-866-467-2748

SEVERE COLD + FLU NIGHTTIME

Drug Facts

ACTIVE INGREDIENT

PURPOSE

Active ingredients (in each packet) | Purposes
Acetaminophen 650 mg | Pain reliever/fever reducer
Dextromethorphan hydrobromide 20 mg | Cough suppressant
Doxylamine succinate 12.5 mg | Antihistamine
Phenylephrine hydrochloride 10 mg | Nasal decongestant

Uses

- temporarily relieves these symptoms due to a cold or flu:
  - headache
  - minor aches and pains
  - cough
  - sore throat
  - nasal congestion
  - sinus congestion and pressure
  - runny nose
  - sneezing
- temporarily reduces fever

Warnings

Liver warning

This product contains acetaminophen. Severe liver damage may occur if you take

- more than 5 packets in 24 hours, which is the maximum daily amount for this product
- with other drugs containing acetaminophen
- 3 or more alcoholic drinks every day while using this product

ALLERGY ALERT

- Acetaminophen may cause severe skin reactions. Symptoms may include:

- Skin reddening
- Blisters
- Rash
- Hives
- facial swelling
- asthma (wheezing)
- shock

Is a skin or general allergic reaction occurs, stop use and seek medical help right away

Sore throat warning

If sore throat is severe, persists for more than 2 days, is accompanied or followed by fever, headache, rash, nausea, or vomiting, consult a doctor promptly.

Do not use to sedate children.

Do not use

- with any other drug containing acetaminophen (prescription or nonprescription). If you are not sure whether a drug contains acetaminophen, ask a doctor or pharmacist.
- if you are now taking a prescription monoamine oxidase inhibitor (MAOI) (certain drugs for depression, psychiatric, or emotional conditions, or Parkinson's disease), or for 2 weeks after stopping the MAOI drug. If you do not know if your prescription drug contains an MAOI, ask a doctor or pharmacist before taking this product.
- if you have ever had an allergic reaction to this product or any of its ingredients
- in children under 12 years of age

Ask a doctor before use if you have

- liver disease
- heart disease
- high blood pressure
- thyroid disease
- diabetes
- glaucoma
- cough with excessive phlegm (mucus)
- a breathing problem such as emphysema or chronic bronchitis
- difficulty in urination due to enlargement of the prostate gland
- persistent or chronic cough such as occurs with smoking, asthma, or emphysema

Ask a doctor or pharmacist before use if you are

- taking the blood thinning drug warfarin
- taking sedatives or tranquilizers

When using this product

- do not exceed recommended dosage
- may cause marked drowsiness
- avoid alcoholic drinks
- alcohol, sedatives, and tranquilizers may increase drowsiness
- be careful when driving a motor vehicle or operating machinery
- excitability may occur, especially in children

Stop use and ask a doctor if

- pain, cough, or nasal congestion gets worse or lasts more than 7 days
- fever gets worse or lasts more than 3 days
- redness or swelling is present
- new symptoms occur
- cough comes back or occurs with rash or headache that lasts. These could be signs of a serious condition.
- nervousness, dizziness, or sleeplessness occurs

PREGNANCY OR BREAST FEEDING

If pregnant or breast-feeding,ask a health professional before use.

Keep out of reach of children.In case of overdose, get medical help or contact a Poison Control Center right away at 1-800-222-1222. Quick medical attention is critical for adults as well as for children even if you do not notice any signs or symptoms.

Directions

- do not take more than the recommended dose
- take every 4 hours; do not exceed 5 packets in 24 hours or as directed by a doctor
- adults and children 12 years and over:dissolve contents of one packet in 8 oz. hot water; sip while hot. Consume entire drink within 10-15 minutes.
- children under 12 years:do not use

Other information

- each packet contains: potassium 6 mg
- store at room temperature

Inactive ingredients

anhydrous citric acid, flavors, maltodextrin, potassium citrate, silica, sucralose, sucrose, yellow#6

Questions or comments?

1-866-467-2748

PRINCIPAL DISPLAY PANEL-

C ompare to Alka-Seltzer PLUS®Severe Cold +Flu Day and Night Active Ingredients*

DAYTIME

SEVERE COLD & FLU

Acetaminophen/ Pain reliever-fever reducer

Dextromethorphan HBr / Cough suppressant

Guaifenesin / Expectorant
Phenylephrine HCl / Nasal decongestant

Relieves:
• Nasal Congestion • Headache
• Sore Throat • Body Ache • Cough
• Mucus • Chest Congestion • Fever

Honey Lemon Flavor

Naturally and Artificially Flavored

NIGHTTIME

Severe Cold & Flu

Acetaminophen/ Pain reliever-fever reducer

Dextromethorphan HBr / Cough suppressant
Doxylamine succinate / Antihistamine
Phenylephrine HCl / Nasal decongestant

Relieves:

• Nasal Congestion • Headache
• Sore Throat • Body Ache
• Cough • Runny Nose • Fever

Honey Lemon Flavor

Naturally and Artificially Flavored

TAMPER EVIDENT: DO NOT USE IF INDIVIDUAL POUCH IS TORN OR OPEN

DO NOT TAKE THESE PRODUCTS AT THE SAME TIME

6 DAY PACKETS + 6 NIGHT PACKETS
12 TOTAL

Distributed by: CVS Pharmacy, Inc.

One CVS Drive Woonsocket, RI 02895

©2017 CVS/pharmacy

CVS.com®1-800-SHOP CVS

Money Back Guarantee

*These products is not manufactured or distributed by Bayer Healthcare, LLC, distributor of Alka-Seltzer plus® Severe Cold +Flu Day and Night.